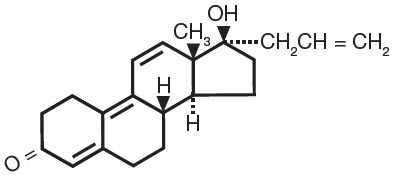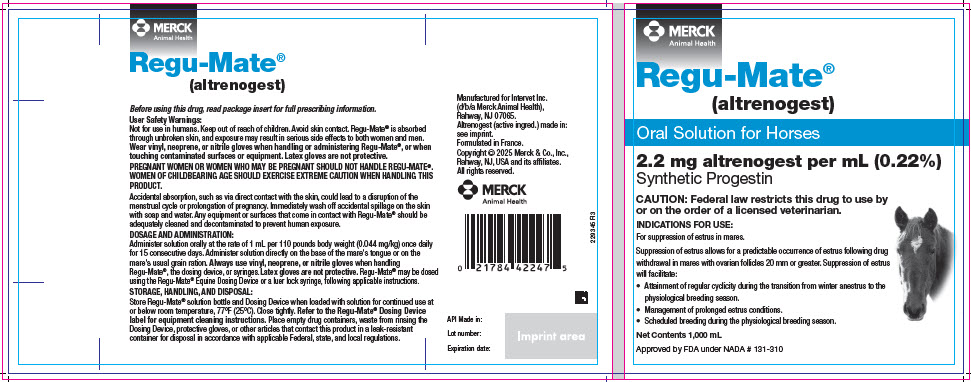 DRUG LABEL: ReguMate
NDC: 57926-100 | Form: SOLUTION
Manufacturer: Merck Sharp & Dohme Corp.
Category: animal | Type: PRESCRIPTION ANIMAL DRUG LABEL
Date: 20250501

ACTIVE INGREDIENTS: ALTRENOGEST 2.2 mg/1 mL

Regu-Mate® (altrenogest)

2.2 mg altrenogest per mL (0.22%)

Oral Solution for Horses

CAUTION:

Federal law restricts this drug to use by or on the order of a licensed veterinarian.

DESCRIPTION:

Regu-Mate® (altrenogest) contains the active synthetic progestin, altrenogest. The chemical name is 17a-allyl-17b-hydroxyestra-4,9,11-trien-3-one. The CAS Registry Number is 850-52-2. The chemical structure is:

Each mL of Regu-Mate® (altrenogest) contains 2.2 mg of altrenogest in an oil solution.

Regu-Mate® (altrenogest) produces a progestational effect in mares.

INDICATIONS:

For suppression of estrus in mares. Suppression of estrus allows for a predictable occurrence of estrus following drug withdrawal. This facilitates the attainment of regular cyclicity during the transition from winter anestrus to the physiological breeding season. Suppression of estrus will also facilitate management of prolonged estrus conditions. Suppression of estrus may be used to facilitate scheduled breeding during the physiological breeding season.

DOSAGE AND ADMINISTRATION:

Administer solution orally at the rate of 1 mL per 110 pounds body weight (0.044 mg/kg) once daily for 15 consecutive days. Administer solution directly on the base of the mare's tongue or on the mare's usual grain ration.

Dosage Chart
Approximate Weight (Pounds) | Dose in mL
770 | 7
880 | 8
990 | 9
1100 | 10
1210 | 11
1320 | 12

When handling Regu-Mate® product, the dosing device, or syringes, always use vinyl, neoprene, or nitrile gloves. Latex gloves are not protective. The product may be dosed using Regu-Mate® Equine Dosing Device or a luer lock syringe. Use of the Regu-Mate® Equine Dosing Device is recommended to reduce the risk of human exposure. Follow all instructions when using the dosing device. Do not use any dosing device other than the Regu-Mate® Equine Dosing Device.

For use with Regu-Mate® Equine Dosing Device, first assemble the device according to directions supplied with the Regu-Mate Equine Dosing Device. Remove the shipping cap and seal on Regu-Mate (altrenogest) bottle. Store the cap in a clean and dry location. Apply downward force and fasten the quick connect cap with dip tube onto the product bottle. The flexible dip tube will contact the bottom of the product bottle and bend slightly. Turn the dose selection dial to 15. Hold the dosing device vertically with the nozzle on the top. Direct the opening of the nozzle away from any person and cover it with absorbent material. Slowly squeeze and release handle until air in the barrel is expelled and product starts to come out. Prime the device by expelling two (2) doses of 15 mL of product into a waste container or absorbent material. (Re-prime the dosing device by expelling two (2) doses if air is observed inside the barrel after switching to a fresh bottle or during dosing period). Set the dose according to DOSAGE CHART provided herein by turning the dose selection dial. The dosing device is ready for use. Refer to the Regu-Mate® Equine Dosing Device label for equipment cleaning instructions.

For use with a luer lock syringe, remove shipping cap and seal; replace with enclosed plastic dispensing cap. Remove cover from bottle dispensing tip and connect luer lock syringe (without needle). Draw out appropriate volume of Regu-Mate® solution and return bottle to upright position before detaching syringe. (Note: Do not remove syringe while bottle is inverted as spillage may result.) Replace cover on bottle dispensing tip to prevent leakage. Syringes used for administration should be replaced frequently and disposed of in a secure manner to prevent exposure to the product.

Which mares will respond to Regu-Mate® (altrenogest):

Extensive clinical trials have demonstrated that estrus will be suppressed in approximately 95% of the mares within three days; however, the post-treatment response depended on the level of ovarian activity when treatment was initiated. Estrus in mares exhibiting regular estrus cycles during the breeding season will be suppressed during treatment; these mares return to estrus four to five days following treatment and continue to cycle normally. Mares in winter anestrus with small follicles continued in anestrus and failed to exhibit normal estrus following withdrawal.

Response in mares in the transition phase between winter anestrus and the summer breeding season depended on the degree of follicular activity. Mares with inactive ovaries and small follicles failed to respond with normal cycles post-treatment, whereas a higher proportion of mares with ovarian follicles 20 mm or greater in diameter exhibited normal estrus cycles post-treatment. Regu-Mate® (altrenogest) was very effective for suppressing the prolonged estrus behavior frequently observed in mares during the transition period (February, March, and April). In addition, a high proportion of these mares responded with regular estrus cycles post-treatment.

Specific Uses for Regu-Mate®:

1. Suppression of estrus to facilitate attainment of regular cycles during the transition period from winter anestrus to the physiological breeding season. To facilitate attainment of regular cycles during the transition phase, mares should be examined to determine the degree of ovarian activity. Estrus in mares with inactive ovaries (no follicles greater than 20 mm in diameter) will be suppressed, but these mares may not begin regular cycles following treatment. However, mares with active ovaries (follicles greater than 20 mm in diameter) frequently respond with regular post-treatment estrus cycles.
2. Suppression of estrus to facilitate management of the mare exhibiting prolonged estrus during the transition period. Estrus will be suppressed in mares exhibiting prolonged behavioral estrus either early or late during the transition period. Again, the post-treatment response depends on the level of ovarian activity. The mares with greater ovarian activity initiate regular cycles and conceive sooner than the inactive mares. Regu-Mate® (altrenogest) may be administered early in the transition period to suppress estrus in mares with inactive ovaries to aid in the management of these mares or to mares later in the transition period with active ovaries to prepare and schedule the mare, for breeding.
3. Suppression of estrus to permit scheduled breeding of mares during the physiological breeding season. To permit scheduled breeding, mares which are regularly cycling or which have active ovarian function should be given Regu-Mate® (altrenogest) daily for 15 consecutive days beginning 20 days before the date of the planned estrus. Ovulation will occur 5 to 7 days following the onset of estrus as expected for non-treated mares. Breeding should follow usual procedures for mares in estrus. Mares may be regulated and scheduled either individually or in groups.

CONTRAINDICATIONS:

Do not use Regu-Mate® (altrenogest) in mares having a previous or current history of uterine inflammation (e.g., acute, subacute, or chronic endometritis). Natural or synthetic gestagen therapy may exacerbate existing low-grade or "smoldering" uterine inflammation into a fulminating uterine infection in some instances.

WARNINGS AND PRECAUTIONS:

User Safety Warnings:

Not for use in humans. Keep out of reach of children. Avoid skin contact. Regu-Mate® is absorbed through unbroken skin, and exposure may result in serious side effects to both women and men. Wear vinyl, neoprene, or nitrile gloves when handling or administering Regu-Mate®, or when touching contaminated surfaces or equipment. Latex gloves are not protective.

PREGNANT WOMEN OR WOMEN WHO MAY BE PREGNANT SHOULD NOT HANDLE REGU-MATE®. WOMEN OF CHILDBEARING AGE SHOULD EXERCISE EXTREME CAUTION WHEN HANDLING THIS PRODUCT.

Accidental absorption, such as via direct contact with the skin, could lead to a disruption of the menstrual cycle or prolongation of pregnancy. Immediately wash off accidental spillage on the skin with soap and water. Any equipment or surfaces that come in contact with Regu-Mate® should be adequately cleaned and decontaminated to prevent human exposure (see Reported HUMAN Effects from Exposure).

Potential Effects of Human Exposure

There has been no human use of this specific product. The information contained in this section is extrapolated from data available on other products of the same pharmacological class that have been used in humans. Effects anticipated are due to the progestational activity of altrenogest.

Acute effects after a single exposure are possible; however, continued daily exposure has the potential for more untoward effects such as disruption of the menstrual cycle, uterine or abdominal cramping, increased or decreased uterine bleeding, prolongation of pregnancy, and headaches. The oil base may also cause complications if swallowed.

The list of people who should not handle this product (see below) is based upon the known effects of progestins used in humans on a chronic basis.

PEOPLE WHO SHOULD NOT HANDLE REGU-MATE®:

1. Women who are or may be pregnant.
2. Anyone with blood clots or clotting disorders, or with a history of these events.
3. Anyone with a history of heart disease or stroke.
4. Women with known or suspected breast cancer.
5. People with known or suspected estrogen-dependent cancer.
6. Women with vaginal bleeding of unknown cause.
7. People with tumors which developed during the use of oral contraceptives or other estrogen-containing products.
8. Anyone with liver dysfunction or disease.

ACCIDENTAL EXPOSURE:

Regu-Mate® is readily absorbed through the skin. In addition, this oil-based product can penetrate latex or other types of porous gloves. Always wear vinyl, neoprene, or nitrile gloves when handling Regu-Mate®. Latex gloves are not protective. If Regu-Mate® gets inside gloves by damage or spilling, the covered skin may absorb more of the drug.

IN CASE OF ACCIDENTAL EXPOSURE:

Skin Exposure and/or clothing contamination: Wash skin immediately with soap and water, and launder clothing with detergent.

Eye Exposure: Immediately flush with plenty of water for 15 minutes. Get medical attention. If wearing contact lenses, flush eyes immediately with water before removing lenses.

If Swallowed: Do not induce vomiting. Seek medical attention immediately. Regu-Mate® contains an oil. Vomiting should be supervised by a physician because of possible pulmonary damage via aspiration of the oil base. If possible, bring the labeling to the physician.

Reported HUMAN Effects from Exposure:

These symptoms have been reported in women and men following accidental exposure to altrenogest products, including Regu-Mate®, either through handling of the product or contact with contaminated surfaces:

- Adverse reproductive effects reported in women included abnormal or absent menstrual cycles.
- Adverse reproductive effects reported in men included decreased libido.
- Other adverse effects reported in women and men included headaches, fever, abdominal pain, nausea, diarrhea, vomiting, and rashes.

ANIMAL SAFETY WARNINGS AND PRECAUTIONS:

Keep Regu-Mate® in a secure location out of reach of dogs, cats, and other animals to prevent accidental ingestion or overdose.

Various synthetic progestins, including altrenogest, when administered to rats during the embryogenic stage of pregnancy at doses manyfold greater than the recommended equine dose, caused fetal anomalies, specifically masculinization of the female genitalia.

OTHER WARNINGS:

Do not use in horses intended for human consumption.

CONTACT INFORMATION:

- To report suspected adverse events, contact Merck at 1-866-349-3497, or www.merck-animal-health-usa.com
- To obtain product information, including safety data sheet (SDS), call 1-800-441-8272.
- For additional information about reporting adverse drug experiences for animal drugs, contact FDA at 1-888-FDA-VETS or www.fda.gov/reportanimalae

REPRODUCTIVE SAFETY STUDY:

A 3-year well-controlled reproductive safety study was conducted in 27 pregnant mares, and compared with 24 untreated control mares. Treated mares received 2 mL Regu-Mate® (altrenogest) /110 lb body weight (2 x dosage recommended for estrus suppression) from day 20 to day 325 of gestation. This study provided the following data:

1. In filly offspring (all ages) of treated mares, clitoral size was increased.
2. Filly offspring from treated mares had shorter interval from Feb. 1 to first ovulation than fillies from their untreated mare counterparts.
3. There were no significant differences in reproductive performance between treated and untreated animals (mares & their respective offspring) measuring the following parameters:
  - interval from Feb. 1 to first ovulation, in mares only.
  - mean interovulatory interval from first to second cycle and second to third cycle, mares only.
  - follicle size, mares only.
  - at 50 days gestation, pregnancy rate in treated mares was 81.8% (9/11) and untreated mares was 100% (4/4).
  - after 3 cycles, 11/12 treated mares were pregnant (91.7 %) and 4/4 untreated mares were pregnant (100%).
  - colt offspring of treated and control mares reached puberty at approximately the same age (82 & 84 weeks respectively).
  - stallion offspring from treated and control mares showed no differences in seminal volume, spermatozoal concentration, spermatozoal motility, and total sperm per ejaculate.
  - stallion offspring from treated and control mares showed no difference in sexual behavior.
  - testicular characteristics (scrotal width, testis weight, parenchymal weight, epididymal weight and height, testicular height, width, & length) were the same between stallion offspring of treated and control mares.

References:

Shoemaker, C.F., E.L. Squires, and R.K. Shideler. 1989. Safety of Altrenogest in Pregnant Mares and on Health and Development of Offspring. Eq. Vet. Sci. (9); No. 2: 69-72.

Squires, E.L., R.K. Shideler, and A.O. McKinnon. 1989. Reproductive Performance of Offspring from Mares Administered Altrenogest During Gestation. Eq. Vet. Sci. (9); No. 2: 73-76.

HOW SUPPLIED:

Regu-Mate® (altrenogest) contains 2.2 mg/mL in an oil solution.

Product supplied in 1,000 mL plastic bottles.

Regu-Mate® Equine Dosing Device supplied separately.

STORAGE, HANDLING, AND DISPOSAL:

Store Regu-Mate® solution bottle and Dosing Device when loaded with solution for continued use at or below room temperature, 77°F (25°C). Close tightly. Refer to the Regu-Mate ® Equine Dosing Device label for equipment cleaning instructions. Place empty drug containers, waste from rinsing the Dosing Device, protective gloves, or other articles that contact this product in a leak-resistant container for disposal in accordance with applicable Federal, state, and local regulations.

Approved by FDA under NADA # 131-310

Restricted Drug (California) - use only as directed.

Manufactured for
Intervet Inc. (d/b/a Merck Animal Health), Rahway, NJ 07065.

Rev. 01/2025

MERCK
Animal Health

PRINCIPAL DISPLAY PANEL - 1,000 mL Bottle Label

MERCK
Animal Health

Regu-Mate®
(altrenogest)

Oral Solution for Horses

2.2 mg altrenogest per mL (0.22%)

Synthetic Progestin

CAUTION: Federal law restricts this drug to use by
or on the order of a licensed veterinarian.

INDICATIONS FOR USE:
For suppression of estrus in mares.

Suppression of estrus allows for a predictable occurrence of estrus following drug
withdrawal in mares with ovarian follicles 20 mm or greater. Suppression of estrus
will facilitate:

- Attainment of regular cyclicity during the transition from winter anestrus to the
  physiological breeding season.
- Management of prolonged estrus conditions.
- Scheduled breeding during the physiological breeding season.

Net Contents 1,000 mL

Approved by FDA under NADA # 131-310